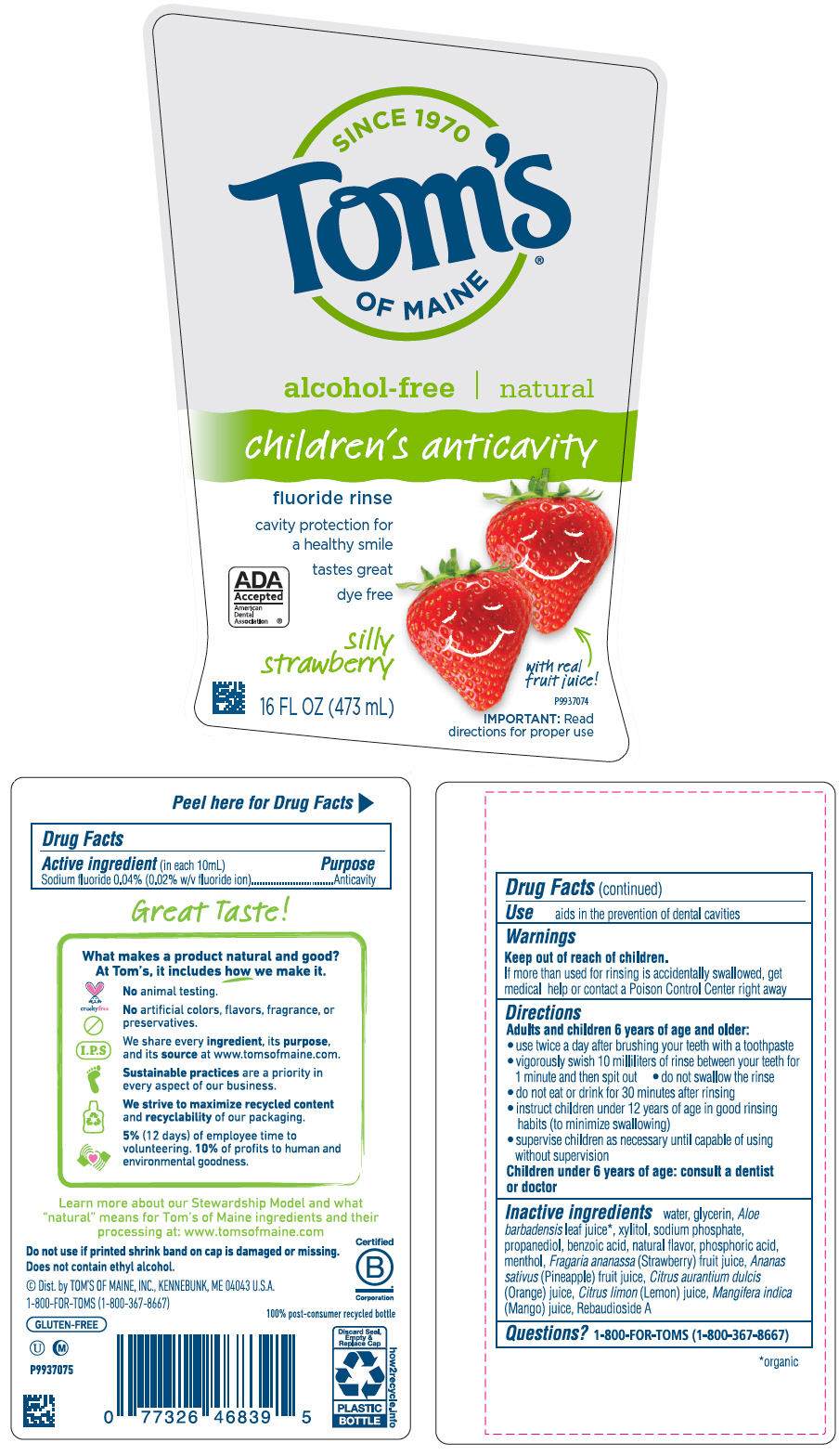 DRUG LABEL: Toms Childrens Anticavity Mouthwash Silly Strawberry
NDC: 51009-840 | Form: RINSE
Manufacturer: Tom's of Maine, Inc.
Category: otc | Type: HUMAN OTC DRUG LABEL
Date: 20240118

ACTIVE INGREDIENTS: SODIUM FLUORIDE 2 mg/10 mL
INACTIVE INGREDIENTS: WATER; GLYCERIN; PROPANEDIOL; XYLITOL; SODIUM PHOSPHATE; BENZOIC ACID; ALOE VERA LEAF; LEVOMENTHOL; PHOSPHORIC ACID; STRAWBERRY JUICE; PINEAPPLE JUICE; ORANGE JUICE; LEMON JUICE; MANGO JUICE; REBAUDIOSIDE A

Tom's Children's Anticavity Mouthwash Silly Strawberry

Drug Facts

Active ingredient (in each 10mL)

Sodium fluoride 0.04% (0.02% w/v fluoride ion)

Purpose

Anticavity

Use

aids in the prevention of dental cavities

Warnings

Keep out of reach of children.

If more than used for rinsing is accidentally swallowed, get medical help or contact a Poison Control Center right away

Directions

Adults and children 6 years of age and older:

- use twice a day after brushing your teeth with a toothpaste
- vigorously swish 10 milliliters of rinse between your teeth for 1 minute and then spit out
- do not swallow the rinse
- do not eat or drink for 30 minutes after rinsing
- instruct children under 12 years of age in good rinsing habits (to minimize swallowing)
- supervise children as necessary until capable of using without supervision

Children under 6 years of age: consult a dentist or doctor

Inactive ingredients

water, glycerin, Aloe barbadensis leaf juice [organic] , xylitol, sodium phosphate, propanediol, benzoic acid, natural flavor, phosphoric acid, menthol, Fragaria ananassa (Strawberry) fruit juice, Ananas sativus (Pineapple) fruit juice, Citrus aurantium dulcis (Orange) juice, Citrus limon (Lemon) juice, Mangifera indica (Mango) juice, Rebaudioside A

Questions?

1-800-FOR-TOMS (1-800-367-8667)

Dist. by TOM'S OF MAINE, INC., KENNEBUNK, ME 04043 U.S.A.

PRINCIPAL DISPLAY PANEL - 473 mL Bottle Label

SINCE 1970
Tom's
OF MAINE®

alcohol-free | natural

children's anticavity

fluoride rinse

cavity protection for
a healthy smile

tastes great

dye free

ADA
Accepted
American
Dental
Association®

silly
strawberry

16 FL OZ (473 mL)

with real
fruit juice!

P9937074

IMPORTANT: Read
directions for proper use